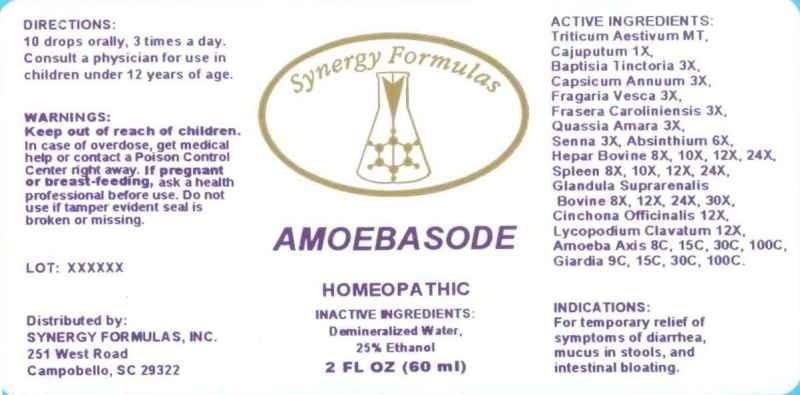 DRUG LABEL: Amoebasode
NDC: 43772-0015 | Form: LIQUID
Manufacturer: Synergy Formulas, Inc.
Category: homeopathic | Type: HUMAN OTC DRUG LABEL
Date: 20130813

ACTIVE INGREDIENTS: TRITICUM AESTIVUM WHOLE 1 [hp_X]/1 mL; CAJUPUT OIL 1 [hp_X]/1 mL; BAPTISIA TINCTORIA 3 [hp_X]/1 mL; CAPSICUM 3 [hp_X]/1 mL; ALPINE STRAWBERRY 3 [hp_X]/1 mL; FRASERA CAROLINIENSIS ROOT 3 [hp_X]/1 mL; QUASSIA AMARA WOOD 3 [hp_X]/1 mL; SENNA LEAF 3 [hp_X]/1 mL; WORMWOOD 6 [hp_X]/1 mL; BEEF LIVER 8 [hp_X]/1 mL; BOS TAURUS SPLEEN 8 [hp_X]/1 mL; BOS TAURUS ADRENAL GLAND 8 [hp_X]/1 mL; CINCHONA OFFICINALIS BARK 12 [hp_X]/1 mL; LYCOPODIUM CLAVATUM SPORE 12 [hp_X]/1 mL; AMOEBA PROTEUS 8 [hp_C]/1 mL; GIARDIA LAMBLIA 9 [hp_C]/1 mL
INACTIVE INGREDIENTS: WATER; ALCOHOL

DRUG FACTS:

ACTIVE INGREDIENTS:

Triticum Aestivum 1X, Cajuputum 1X, Baptisia Tinctoria 3X, Capsicum Annuum 3X, Fragaria Vesca 3X, Frasera CAroliniensis 3X, Quassia Amara 3X, Senna 3X, Absinthium 6X, Hepar Bovine 8X, 10X, 12X, 24X, Spleen (Bovine) 8X, 10X, 12X, 24X, Glandula Suprarenalis Bovine 8X, 12X, 24X, 30X, Cinchona Officinalis 12X, Lycopodium Clavatum 12X, Amoeba Axis 8C, 15C, 30C, 100C, Giardia 9C, 15C, 30C, 100C.

INDICATIONS:

For temporary relief of symptoms of diarrhea, mucus in stools, and intestinal bloating.

WARNINGS:

Keep out of reach of children. In case of overdose, get medical help or contact a Poison Control Center right away.

If pregnant or breast-feeding, ask a health professional before use.

Do not use if tamper evident seal is broken or missing.

DIRECTIONS:

10 drops orally, 3 times a day. Consult a physician for use in children under 12 years of age.

INACTIVE INGREDIENTS:

Demineralized Water, 25% Ethanol

Keep out of reach of children. In case of overdose, get medial help or contact a Poison Control Center right away.

INDICATIONS:

For temporary relief of symptoms of diarrhea, mucus in stools, and intestinal bloating.

QUESTIONS:

Distributed by:

SYNERGY FORMULAS, INC.

251 West Road

Campobello, SC 29322

PACKAGE DISPLAY LABEL:

Synergy Formula

AMOEBASODE

HOMEOPATHIC

2 FL OZ (60 mL)